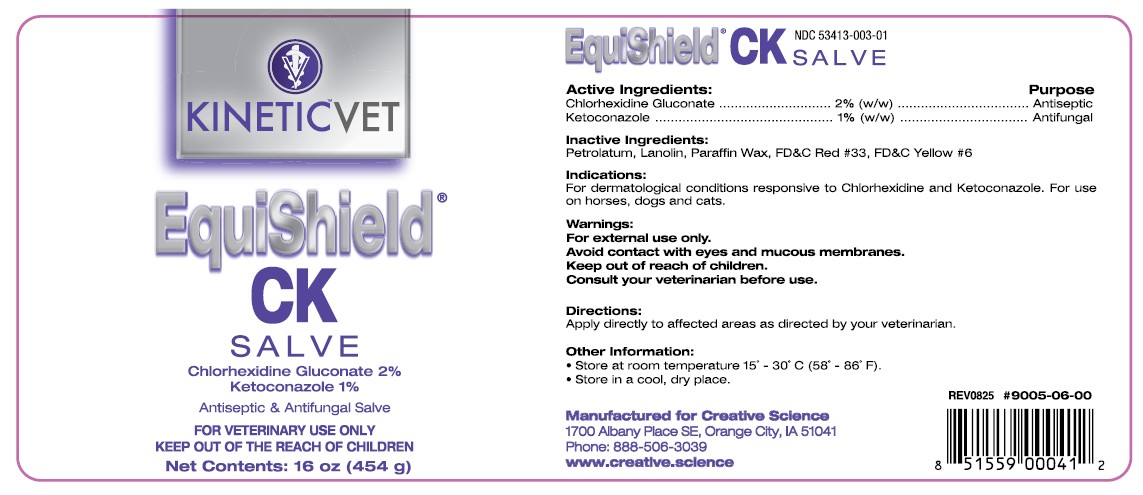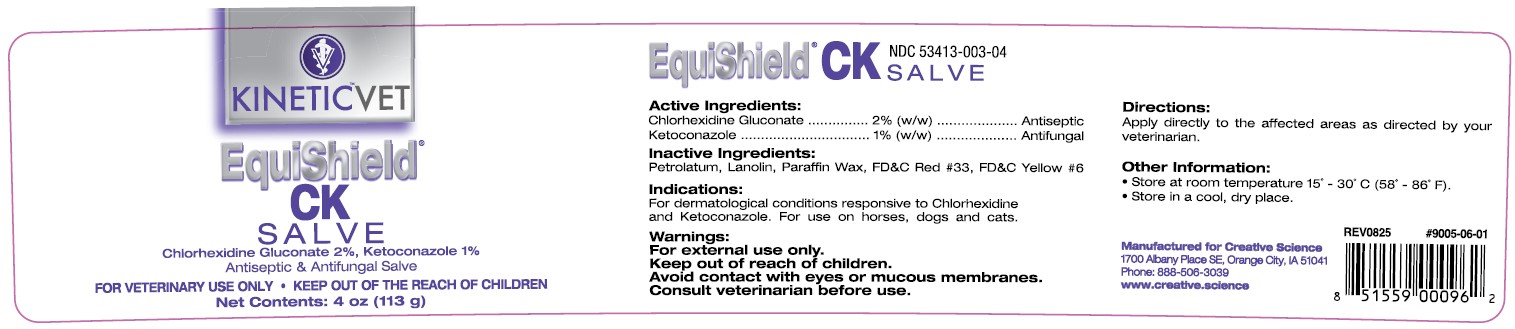 DRUG LABEL: EquiShield CK
NDC: 53413-003 | Form: SALVE
Manufacturer: Creative Science
Category: animal | Type: OTC ANIMAL DRUG LABEL
Date: 20251206

ACTIVE INGREDIENTS: CHLORHEXIDINE GLUCONATE 2 g/100 g; KETOCONAZOLE 1 g/100 g

EquiShield® CK Salve

Active Ingredients:

Chlorhexidine Gluconate ........... 2% (w/w)............ Antiseptic
Ketoconazole ........................... 1% (w/w)........... Antifungal

Inactive Ingredients:

Petrolatum, Lanolin, Paraffin Wax, FD&C Red #33, FD&C Yellow #6

Indications:

For dermatological conditions responsive to Chlorhexidine and Ketoconazole. For use on horses, dogs and cats.

Warnings:

For external use only.

Avoid contact with eyes and mucous membranes.

Keep out of reach of children.

Consult your veterinarian before use.

Directions:

Apply directly to affected areas as directed by your veterinarian.

Other Information:

• Store at room temperature 15˚ - 30˚C (58˚ - 86˚F).
• Store in a cool, dry place.

NDC 53413-003-01 UPC 851559000412 Rev 0825 #9005-06-00 NDC 53413-003-04 UPC 851559000962 Rev 0825 #9005-06-01

Manufactured for Creative Science

1700 Albany Place SE, Orange City, IA 51041

Phone: 888-506-3039

www.creative.science

KINETIC™VET

EquiShield® CK SALVE

Chlorhexidine Gluconate 2%, Ketoconazole 1%

Antiseptic & Antifungal Salve

FOR VETERINARY USE ONLY • KEEP OUT OF THE REACH OF CHILDREN

Net Contents: 4 oz (113 g)

Net Contents: 16 oz (454 g)

CK Salve 4 oz

CK Salve 16 oz